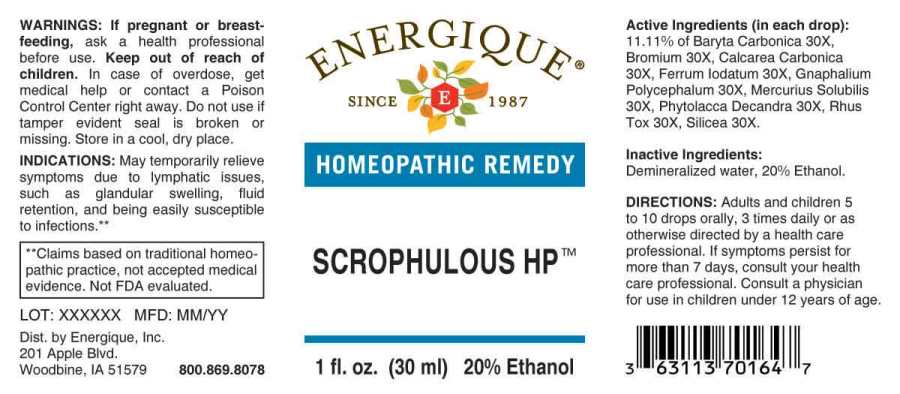 DRUG LABEL: Scrophulous
NDC: 44911-0404 | Form: LIQUID
Manufacturer: Energique, Inc.
Category: homeopathic | Type: HUMAN OTC DRUG LABEL
Date: 20241030

ACTIVE INGREDIENTS: BARIUM CARBONATE 30 [hp_X]/1 mL; BROMINE 30 [hp_X]/1 mL; OYSTER SHELL CALCIUM CARBONATE, CRUDE 30 [hp_X]/1 mL; FERROUS IODIDE 30 [hp_X]/1 mL; PSEUDOGNAPHALIUM OBTUSIFOLIUM 30 [hp_X]/1 mL; MERCURIUS SOLUBILIS 30 [hp_X]/1 mL; PHYTOLACCA AMERICANA ROOT 30 [hp_X]/1 mL; TOXICODENDRON PUBESCENS LEAF 30 [hp_X]/1 mL; SILICON DIOXIDE 30 [hp_X]/1 mL
INACTIVE INGREDIENTS: WATER; ALCOHOL

DRUG FACTS:

ACTIVE INGREDIENTS:

(in each drop): 11.11% of Baryta Carbonica 30X, Bromium 30X, Calcarea Carbonica 30X, Ferrum Iodatum 30X, Gnaphalium Polycephalum 30X, Mercurius Solubilis 30X, Phytolacca Decandra 30X, Rhus Tox 30X, Silicea 30X.

INDICATIONS:

May temporarily relieve symptoms due to lymphatic issues, such as glandular swelling, fluid retention, and being easily susceptible to infections.**

**Claims based on traditional homeopathic practice, not accepted medical evidence. Not FDA evaluated.

WARNINGS:

If pregnant or breastfeeding, ask a health professional before use.

Keep out of reach of children. In case of overdose, get medical help or contact a Poison Control Center right away.

Do not use if tamper evident seal is broken or missing.

Store in a cool, dry place.

Keep out of reach of children. In case of overdose, get medical help or contact a Poison Control Center right away.

DIRECTIONS:

Adults and children 5 to 10 drops orally, 3 times daily or as otherwise directed by a health care professional. If symptoms persist for more than 7 days, consult your health care professional. Consult a physician for use in children under 12 years of age.

INDICATIONS:

May temporarily relieve symptoms due to lymphatic issues, such as glandular swelling, fluid retention, and being easily susceptible to infections.**

**Claims based on traditional homeopathic practice, not accepted medical evidence. Not FDA evaluated.

INACTIVE INGREDIENTS:

Demineralized water, 20% Ethanol.

QUESTIONS:

Dist. by Energique, Inc.
201 Apple Blvd.
Woodbine, IA 51579 800.869.8078

PACKAGE LABEL DISPLAY:

ENERGIQUE
SINCE 1987
HOMEOPATHIC REMEDY
SCROPHULOUS HP
1 fl. oz. (30 ml)